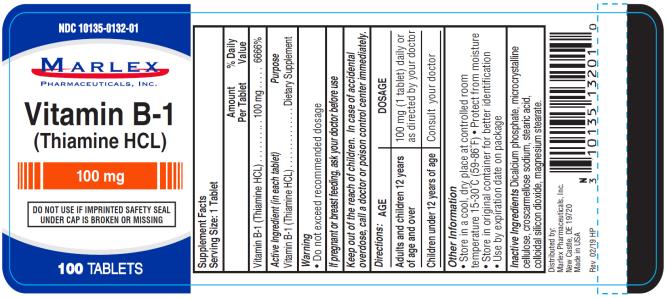 DRUG LABEL: Thiamine HCL 100 mg
NDC: 10135-132 | Form: TABLET
Manufacturer: Marlex Pharmaceuticals Inc
Category: other | Type: DIETARY SUPPLEMENT
Date: 20200228

ACTIVE INGREDIENTS: THIAMINE 100 mg/1 1
INACTIVE INGREDIENTS: ANHYDROUS DIBASIC CALCIUM PHOSPHATE; MICROCRYSTALLINE CELLULOSE; CROSCARMELLOSE SODIUM; STEARIC ACID; SILICON DIOXIDE; MAGNESIUM STEARATE

Thiamine HCL 100 mg

Supplement Facts

Serving Size: 1 Tablet

Amount %Daily
Per Tablet Value

Vitamin B-1(Thiamine HCL).…………….…100mg……………….6666%

Vitamin B-1 (Thiamine HCL) 100mg Dietary Supplement

Active Ingredient (in each tablet)

Vitamin B-1 (Thiamine HCL)

Purpose

Dietary Supplement

Warnings

- Do not exceed recommended dosage

If pregnant or breast feeding,

Ask your doctor before use.

Keep out of reach of children.

In case of accidental overdose, call a doctor or poison control center immediately.

Directions:

AGE | DOSAGE
Adults and children 12 years of age and over | 100mg (1 tablet) daily or as directed by your doctor
Children under 12 years of age | Consult your doctor

Other Information:

- Store in a cool, dry place at controlled room temperature 15-30◦C (59-86◦F)
- Protect from moisture
- Store in original container for better identification
- Use by expiration date on package

Inactive Ingredients:

Dicalcium phosphate, microcrystalline cellulose, Croscarmellose sodium, stearic acid, colloidal silicon dioxide, magnesium stearate.

Manufactured for & Distributed by:

Marlex Pharmaceuticals, Inc.

New Castle, DE 19720

Rev: 02/19 HP

PRINCIPAL DISPLAY PANEL

NDC 10135-0132-01
Vitamin B-1
(Thiamine HCL)
100 mg
100 TABLETS